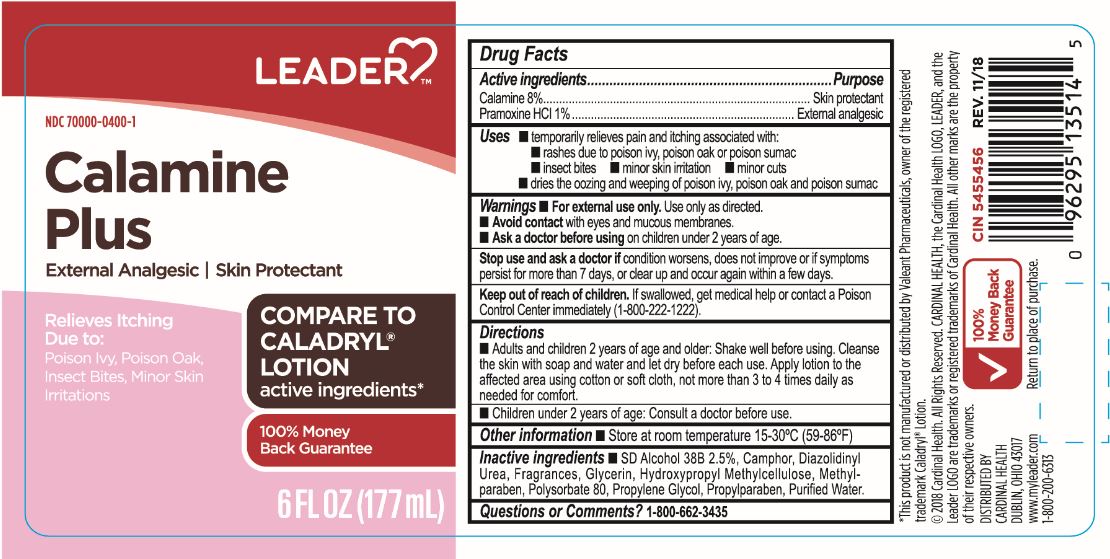 DRUG LABEL: Leader Calamine Plus
NDC: 70000-0400 | Form: LOTION
Manufacturer: Cardinal Health, 110 dba Leader
Category: otc | Type: HUMAN OTC DRUG LABEL
Date: 20231222

ACTIVE INGREDIENTS: ZINC OXIDE 80 mg/1 mL; PRAMOXINE HYDROCHLORIDE 10 mg/1 mL
INACTIVE INGREDIENTS: ALCOHOL; CAMPHOR (SYNTHETIC); DIAZOLIDINYL UREA; PROPYLENE GLYCOL; HYPROMELLOSES; GLYCERIN; METHYLPARABEN; PROPYLPARABEN; POLYSORBATE 80; WATER

LEADER Calamine Plus

WARNINGS

- For external use only
- Avoid contact with eyes and mucous membranes
- Ask a doctor before using on children under 2 years of age

ACTIVE INGREDIENT

Calamine 8%

Pramoxine HCl 1%

PURPOSE

- Skin Protectant
- External Analgesic

DOSAGE AND ADMINISTRATION

Adults and children 2 years of age and older: Shake well before using. CLeanse the skin with soap and water and let dry before each use. Apply lotion to the affected area using cotton of soft cloth, not more than 3 to 4 times daily as needed for comfort.

Children under 2 years of age: Consult a doctor before use.

INACTIVE INGREDIENT

SH Alcohol 38B 2.5%

Camphor

Diazolidinyl Urea

Fragrances

Glycerin

Hydroxypropyl Methylcellulose

Methylparaben

Polysorbate 80

Propylene Glycol

Propylparabaren

Purified water

Keep out of reach of children. If swallowed, get medical help or contact a Poison Control Center immediately (1-800-222-1222)

Uses:
temporarily relieves pain and itching associated with:

- rashes due to poison ivy, poison oak, or poison sumac
- insect bites
- minor skin irritation
- minor cuts
- dries the oozing and weeping of poison ivy, poison oak and poison sumac